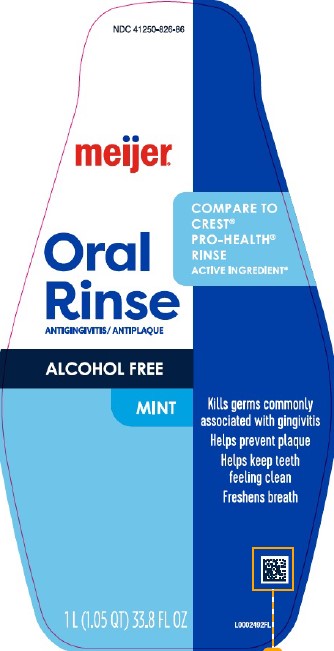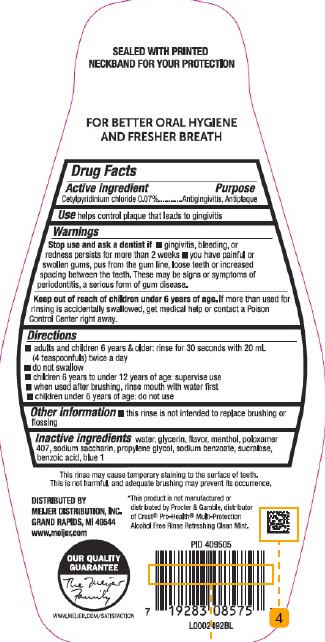 DRUG LABEL: Mint
NDC: 41250-826 | Form: MOUTHWASH
Manufacturer: Meijer, Inc.
Category: otc | Type: HUMAN OTC DRUG LABEL
Date: 20260219

ACTIVE INGREDIENTS: CETYLPYRIDINIUM CHLORIDE 0.7 mg/1 mL
INACTIVE INGREDIENTS: WATER; GLYCERIN; MENTHOL, UNSPECIFIED FORM; POLOXAMER 407; SACCHARIN SODIUM; PROPYLENE GLYCOL; SODIUM BENZOATE; SUCRALOSE; BENZOIC ACID; FD&C BLUE NO. 1

Meijer 299.006/299AM
Multi Action Alcohol Free Antiseptic Rinse w/CPC

Tamper Evident Statement

Sealed with printed neckband for your protection

Claim

FOR BETTER ORAL HYGIENE AND FRESHER BREATH

Active Ingredient

Cetylpyridinium chloride 0.07%

Purpose

Antigingivitis, Antiplaque

Use

helps control plaque that leads to gingivitis

Warnings

for this product

Stop use and ask a dentist if

- gingivitis, bleeding, or redness persists for more than 2 weeks
- you have painful or swollen gums, pus from the gum line, loose teeth or increased spacing between the teeth. These may be signs or symptoms of periodontitis, a serious form of gum disease..

Keep out of reach of children under 6 years of age.

If more than used for rinsing is accidentally swallowed, get medical help or contact a Poison Control Center right away.

Directions

- adults and children 6 years & older: rinse for 30 seconds with 20 mL (4 teaspoonfuls) twice a day
- do not swallow
- children 6 years to under 12 years of age: supervise use
- when used after brushing, rinse mouth with water first
- children under 6 years of age: do not use

Other information

- this rinse is not intended to replace brushing or flossing

Inactive ingredients

water, glycerin, flavor, menthol, poloxamer 407, sodium saccharin, propylene glycol, sodium benzoate, sucralose, benzoic acid, blue 1

Disclaimers

This rinse may cause temporary staining to the surface of teeth.

This is not harmful, and adequate brushing may prevent its occurrence.

*This product is not manufactured or distributed by Procter & Gamble, distributor of Crest Pro-Health® Multi-Protection Alcohol Free Rinse Refreshing Clean Mint.

Adverse Reaction

DISTRIBUTED BY

MEIJER DISTRIBUTION, INC.

GRAND RAPIDS, MI 49544

www.meijer.com

OUR QUALITY GUARANTEE

The Meijer Family

WWW.MEIJER.COM/SATISFACTION

Principal display panel

NDC 41250-826-86

meijer®

COMPARE TO CREST®PRO-HEALTH® RINSE ACTIVE INGREDIENT*

Oral Rinse

ANTIGINGIVITIS/ANTIPLAQUE

ALCOHOL FREE

MINT

Kills germs commonly associated with gingivitis

Helps prevent plaque

Helps keep teeth feeling clean

Freshens breath

1L (1.05 QT) 33.8 FL OZ